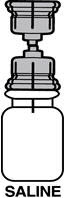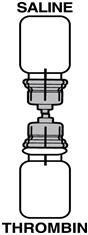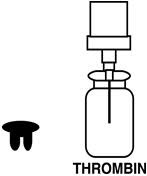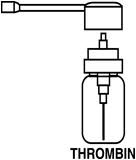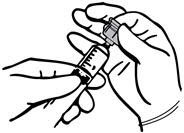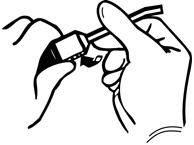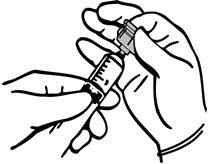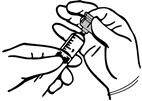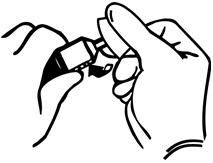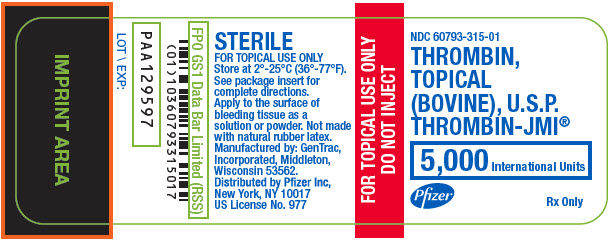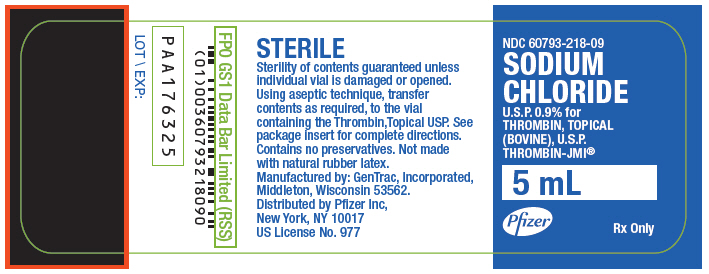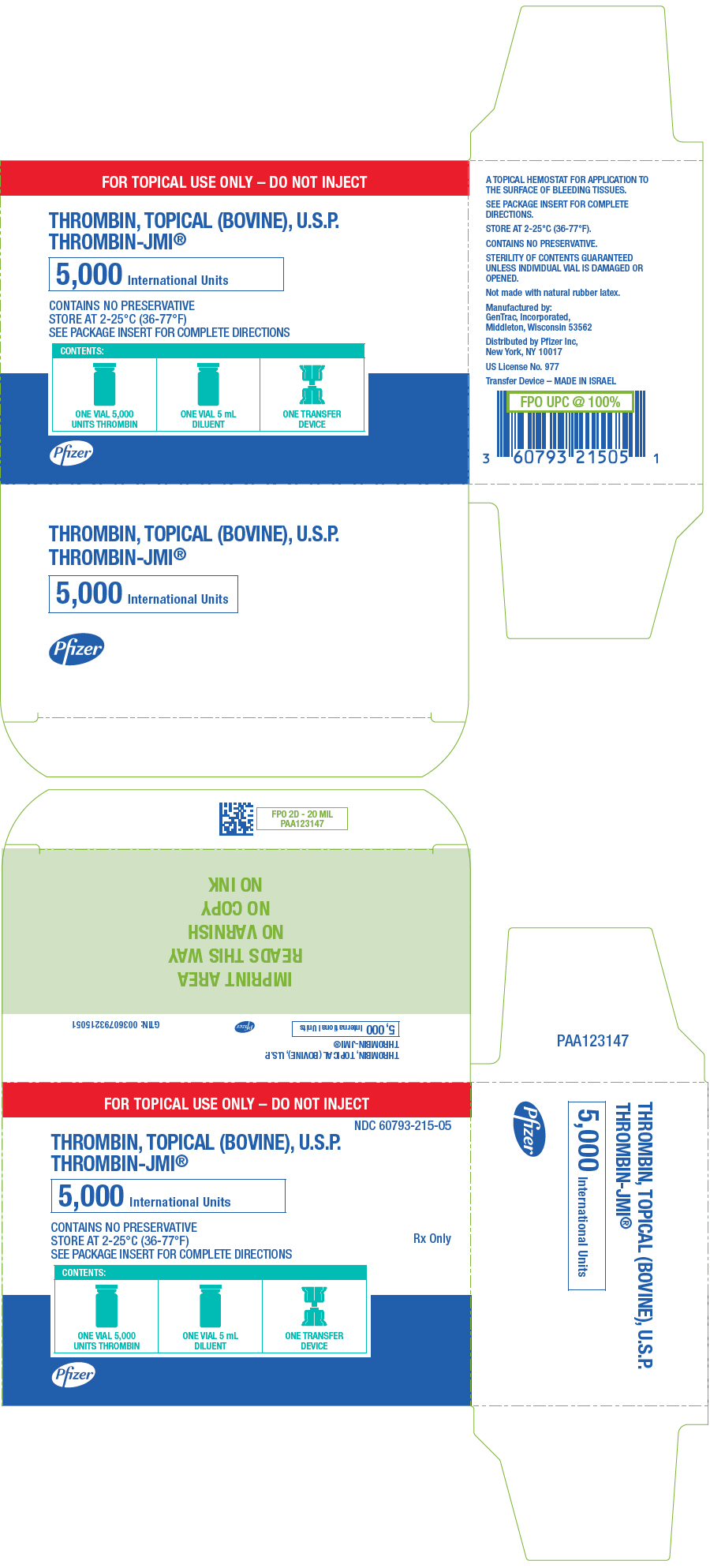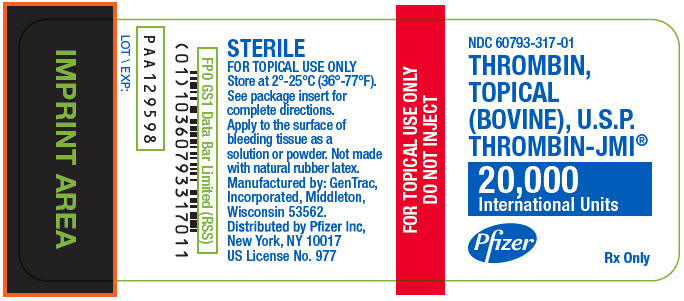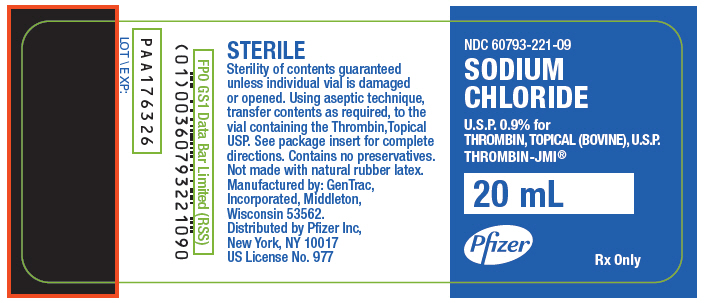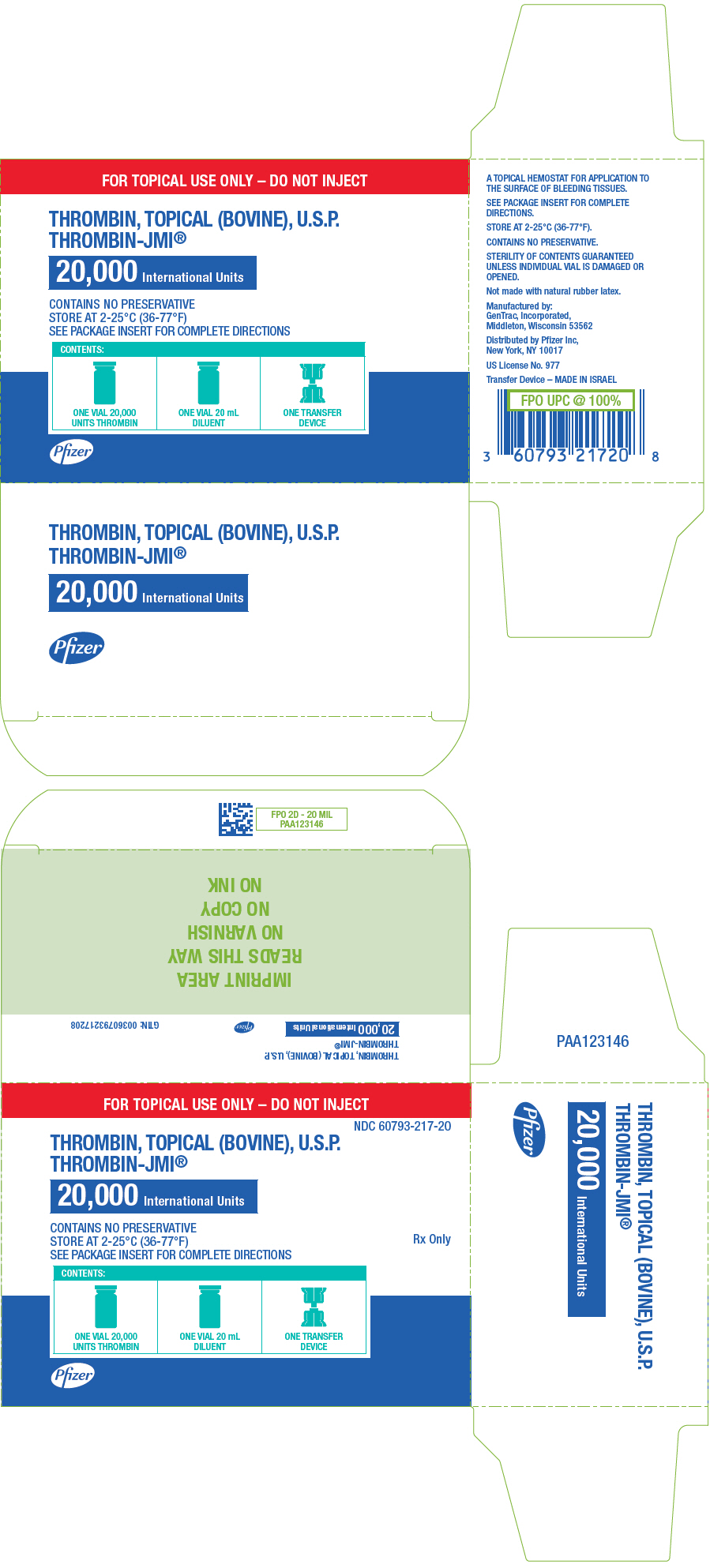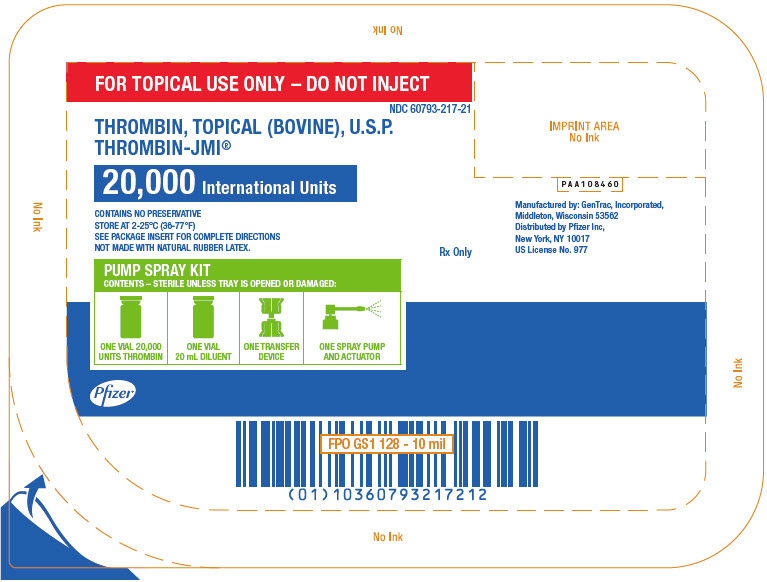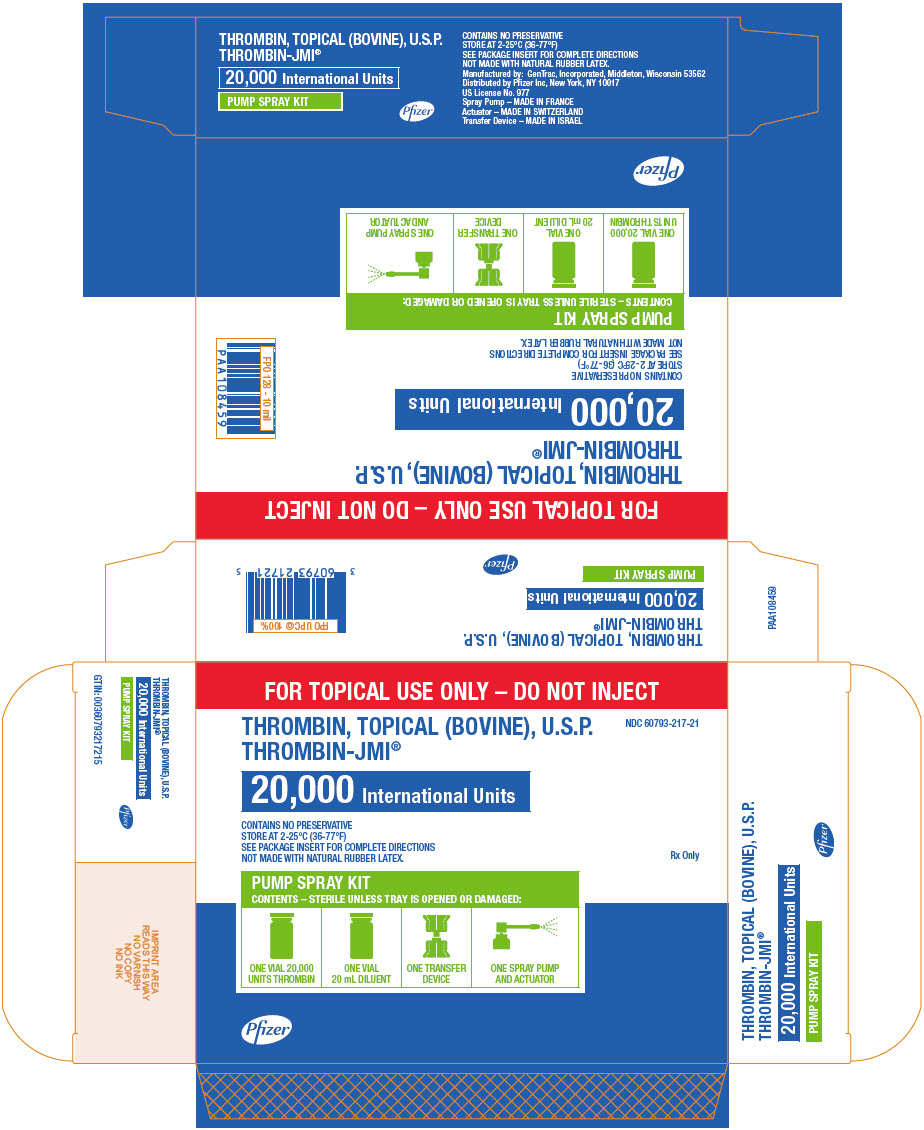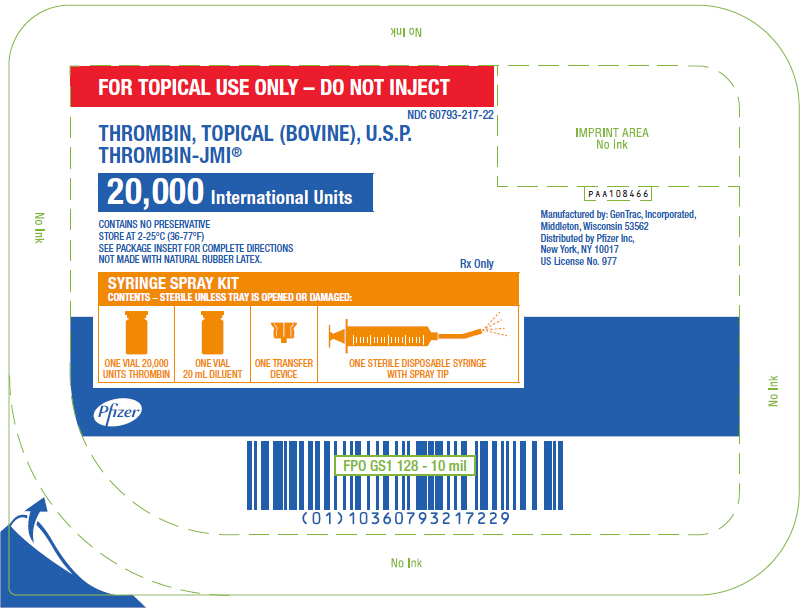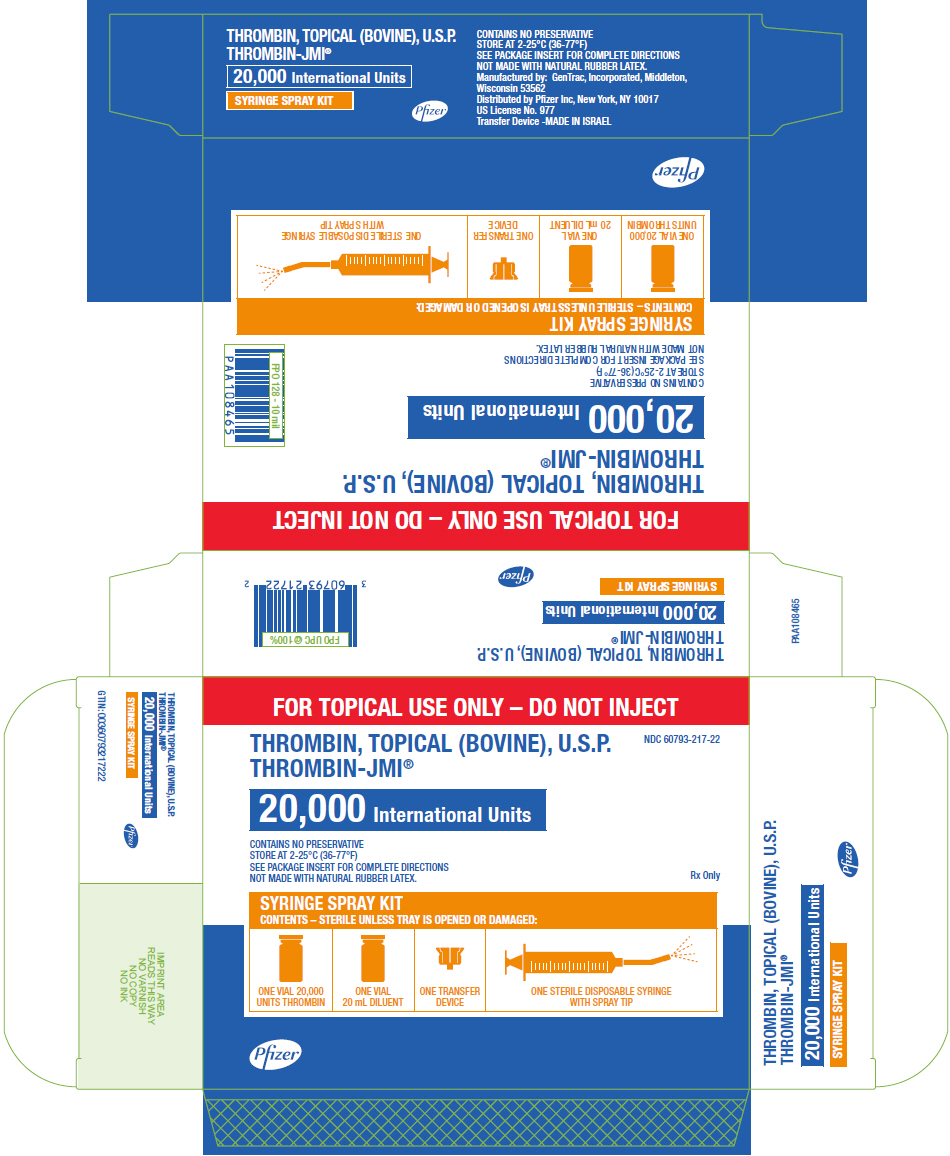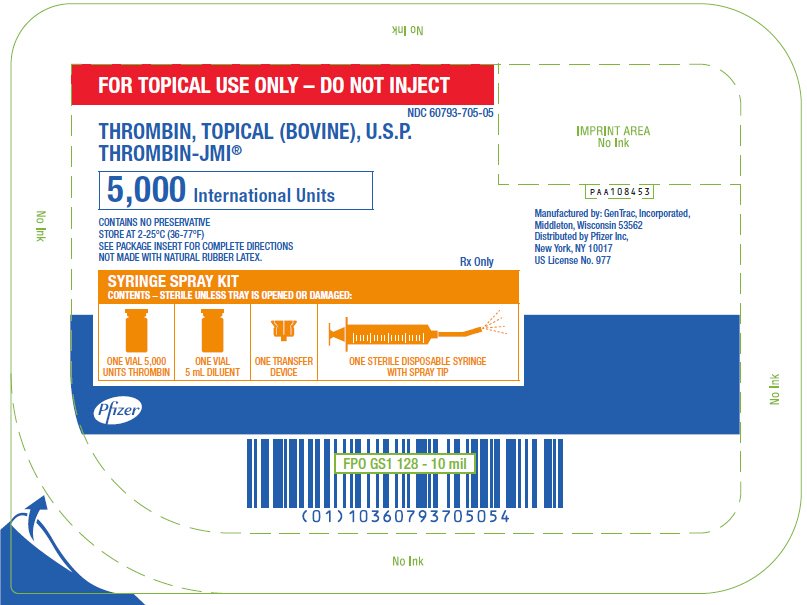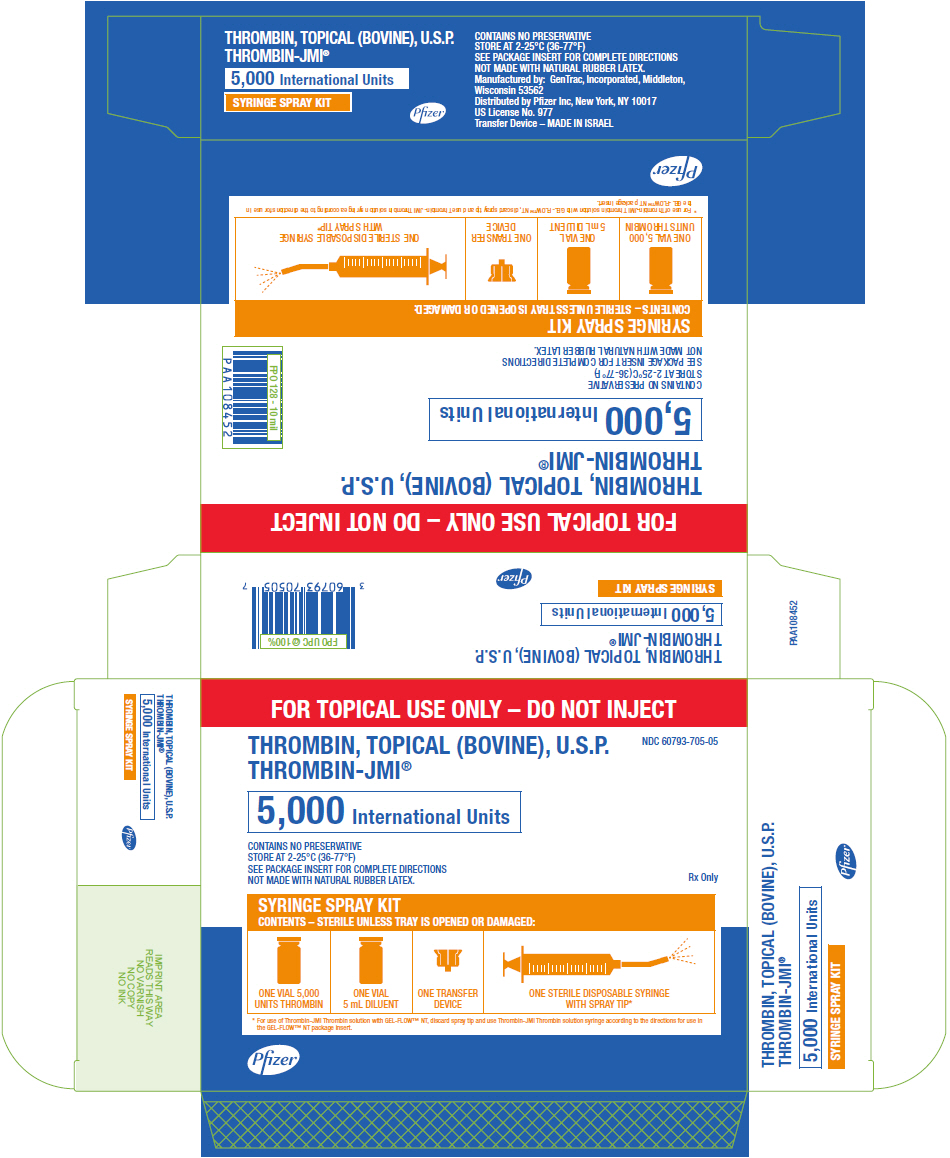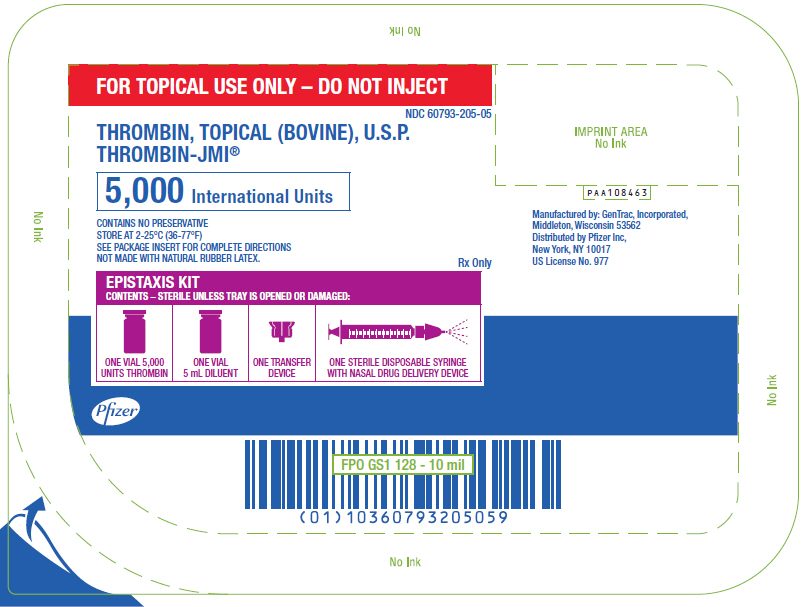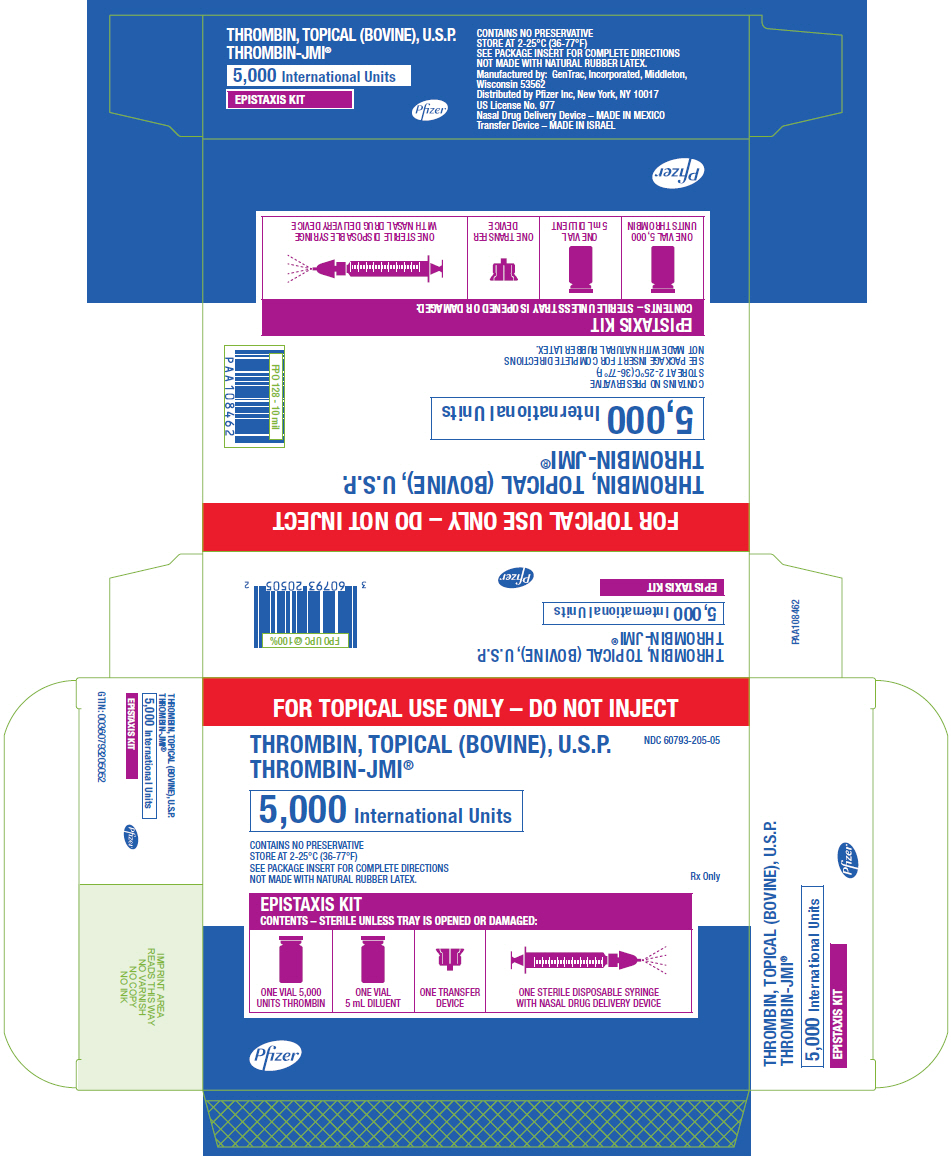 DRUG LABEL: THROMBIN-JMI
NDC: 60793-215 | Form: KIT | Route: TOPICAL
Manufacturer: Pfizer Laboratories Div Pfizer Inc
Category: other | Type: PLASMA DERIVATIVE
Date: 20251112

ACTIVE INGREDIENTS: THROMBIN 5000 [iU]/5 mL
INACTIVE INGREDIENTS: MANNITOL; SODIUM CHLORIDE; SODIUM CHLORIDE

HIGHLIGHTS OF PRESCRIBING INFORMATION

These highlights do not include all the information needed to use THROMBIN-JMI safely and effectively. See full prescribing information for THROMBIN-JMI.
THROMBIN-JMI® (Thrombin, Topical (Bovine) U.S.P.), Solution for topical use
Initial U.S. Approval: 1986

RECENT MAJOR CHANGES

Warnings and Precautions, Thrombosis (5.2) | 6/2023
Warnings and Precautions, Immunogenicity (5.3) | 6/2023

WARNING: SEVERE BLEEDING AND THROMBOSIS COMPLICATIONS

See full prescribing information for complete boxed warning

- THROMBIN-JMI can cause fatal severe bleeding or thrombosis. Thrombosis may result from the development of antibodies against bovine thrombin. Bleeding may result from the development of antibodies against factor V. These may cross-react with human factor V and lead to its deficiency. (5.2, 5.3)
- Do not re-expose patients to THROMBIN-JMI if there are known or suspected antibodies to bovine thrombin and/or factor V. (4, 5.3)
- Monitor patients for abnormal coagulation laboratory values, bleeding, or thrombosis. (5.3)

1 INDICATIONS AND USAGE

- THROMBIN-JMI is a topical thrombin indicated to aid hemostasis whenever oozing blood and minor bleeding from capillaries and small venules is accessible and control of bleeding by standard surgical techniques (such as suture, ligature, or cautery) is ineffective or impractical. (1)
- THROMBIN-JMI may be used in conjunction with an absorbable gelatin sponge, USP. (1)

2 DOSAGE AND ADMINISTRATION

For topical use on the surface of bleeding tissue only. Do not inject. (2)

- May be reconstituted with sterile isotonic saline at a recommended concentration of 1,000 to 2,000 International Units (IU)/mL or may be used in dry form on oozing surfaces. (2)

3 DOSAGE FORMS AND STRENGTHS

- THROMBIN-JMI is available as 5,000 IU vial with 5 mL diluent and 20,000 IU vial with 20 mL diluent. (3)
- THROMBIN –JMI Pump Spray Kit is available as 20,000 IU vial with 20 mL diluent, spray pump and actuator. (3)
- THROMBIN-JMI Syringe Spray Kit is available as 5,000 IU vial with 5 mL diluent, spray tip and syringe and 20,000 IU vial with 20 mL diluent, spray tip and syringe. (3)
- THROMBIN-JMI Epistaxis Kit is available as 5,000 IU vial with 5 mL diluent, nasal drug delivery device and syringe. (3)
- THROMBIN-JMI is available in the Gelfoam-JMI™ Powder Kit (Gelfoam® Absorbable Gelatin Powder and Thrombin, Topical (Bovine) U.S.P., THROMBIN-JMI®, 5,000 IU vial with 5 mL diluent. (3)
- THROMBIN-JMI is available in the Gelfoam-JMI™ Sponge Kit (Gelfoam® Absorbable Gelatin Sponge, USP and Thrombin, Topical (Bovine) U.S.P., THROMBIN-JMI®, 5,000 IU vial with 5 mL diluent. (3)
- THROMBIN-JMI® 5,000 IU Syringe Spray Kit is supplied in the GEL-FLOW™ Kit: GEL-FLOW™ Kit (GEL-FLOW™ NT Absorbable Gelatin Powder and Thrombin, Topical (Bovine) U.S.P., THROMBIN-JMI®, 5,000 IU Syringe Spray Kit). (3)

4 CONTRAINDICATIONS

- Do not inject directly into the circulatory system. (4, 5.2)
- Do not re-expose patients to THROMBIN-JMI if there are known or suspected antibodies to bovine thrombin and/or factor V. (4, 5.3)
- Do not administer to patients with a history of hypersensitivity to THROMBIN-JMI, its components and/or material of bovine origin. (4, 5.1)
- Do not use for treatment of severe or brisk arterial bleeding. (4)

5 WARNINGS AND PRECAUTIONS

- Allergic reactions, including anaphylactic/anaphylactoid reactions, have been reported following administration of THROMBIN-JMI. (5.1)
- Institute intensive supportive measures and treat individual symptoms. Secure the airway and establish adequate respiratory exchange. (5.1)
- THROMBIN-JMI causes thrombosis if it enters the circulatory system. Apply topically. DO NOT INJECT. (5.2)
- Inhibitory antibodies may develop in patients and interfere with hemostasis. Monitor patients for abnormal coagulation laboratory values, bleeding, or thrombosis. (5.3)

6 ADVERSE REACTIONS

Most common adverse reactions (incidence ≥ 2%) are hypersensitivity, bleeding, anemia, post-operative wound infection, thromboembolic events, hypotension, pyrexia, tachycardia and thrombocytopenia. (6)

To report SUSPECTED ADVERSE REACTIONS, contact Pfizer, Inc. at 1-800-438-1985 or FDA at 1-800-FDA-1088 or www.fda.gov/medwatch.

FULL PRESCRIBING INFORMATION

WARNING: SEVERE BLEEDING AND THROMBOSIS COMPLICATIONS

- THROMBIN-JMI® can cause fatal severe bleeding or thrombosis. Thrombosis may result from the development of antibodies against bovine thrombin. Bleeding may result from the development of antibodies against factor V. These may cross-react with human factor V and lead to its deficiency. (5.2, 5.3)
- Do not re-expose patients to THROMBIN-JMI if there are known or suspected antibodies to bovine thrombin and/or factor V. (4, 5.3)
- Monitor patients for abnormal coagulation laboratory values, bleeding, or thrombosis. (5.3)

1 INDICATIONS AND USAGE

THROMBIN-JMI is topical bovine thrombin indicated to aid hemostasis whenever oozing blood and minor bleeding from capillaries and small venules is accessible and control of bleeding by standard surgical techniques (such as suture, ligature, or cautery) is ineffective or impractical.

In various types of surgeries, solutions of THROMBIN-JMI may be used in conjunction with an Absorbable Gelatin Sponge, USP for hemostasis.

2 DOSAGE AND ADMINISTRATION

For topical use on the surface of bleeding tissue only. Do not inject.

2.1 Reconstitution

- For routine use, reconstitute THROMBIN-JMI with sterile isotonic saline at a recommended concentration of 1,000 to 2,000 IU per mL.
- Where bleeding is profuse, as from abraded surfaces of liver or spleen, concentrations of 1,000 IU per mL may be required.
- For general use in plastic surgery, dental extractions, skin grafting, etc. solutions containing approximately 100 IU per mL are frequently used. Prepare intermediate strengths to suit the needs of the case by diluting the contents of the THROMBIN-JMI container with an appropriate volume of sterile isotonic saline. THROMBIN-JMI can be used in a dry form on oozing surfaces.
- In instances where a concentration of approximately 1,000 IU per mL is desired, the contents of the vial of sterile isotonic saline diluent may be transferred into the THROMBIN-JMI container with a sterile syringe or sterile transfer device.
- For use with GEL-FLOW™ NT, reconstitute THROMBIN-JMI 5,000 IU powder with 5 mL sterile isotonic saline and use THROMBIN-JMI thrombin solution according to the directions for use in the GEL-FLOW™ NT package insert.

If the transfer device is used for reconstitution, transfer the diluent in the following manner:

1. Remove the plastic cap off of the diluent vial.
2. Remove the Tyvek cover from the transfer device container. Do not remove the device from the package.
3. Seat the blue end of the device on the diluent vial, pushing down until the spike penetrates the diaphragm and the device snaps in place.
4. Flip the plastic cover off on the THROMBIN-JMI container. DO NOT REMOVE THE ALUMINUM SEAL.
5. Remove the plastic package from the transfer device. Do not touch the exposed end of the device.
6. Invert the vial of diluent and insert the clear end of the transfer device into the diaphragm of the THROMBIN-JMI container.

CAUTION: Solutions should be used promptly upon removal from the container. However, the solution may be refrigerated at 2°C – 8°C for up to 24 hours, or may be stored at room temperature for up to 8 hours after reconstitution.

THROMBIN-JMI PUMP SPRAY KIT

Refer to THROMBIN-JMI Pump Spray Kit instructions for spray pump assembly and use.

Each spray kit contains one vial of THROMBIN-JMI, one vial of diluent and one spray pump and actuator.

1. Remove the outer lid by pulling up at the indicated edge. The inner tray is sterile and suitable for introduction into any operating field.
2. Remove the cover on inner tray to expose sterile contents.
3. Reconstitute the THROMBIN-JMI to desired potency by introducing sterile isotonic saline with a sterile syringe or a sterile transfer device. If the transfer device is used, follow the previously described procedure.
4. When the THROMBIN-JMI is completely dissolved, open vial by flipping up metal and tearing counterclockwise.
5. Remove the rubber diaphragm from vial. Remove pump with protective cap from tray and snap onto vial.
6. Remove protective cap and attach actuator.
7. To spray, hold vial upright or at a slight angle. Several strokes of the pump will be required to expel the solution.
8. Discard unused contents and pump: DO NOT TRANSFER SPRAY PUMP TO ANOTHER VIAL.

THROMBIN-JMI SYRINGE SPRAY KIT

Refer to THROMBIN-JMI Syringe Spray Kit instructions for spray syringe assembly and use. Each syringe kit contains one vial of THROMBIN-JMI, one vial of diluent and one spray tip and syringe.

1. Remove the outer lid by pulling up at the indicated edge. The inner tray is sterile and suitable for introduction into any operating field.
2. Remove the cover on the inner tray to expose sterile contents.
3. Using the sterile syringe equipped with a transfer device, draw the desired amount of saline diluent from the vial into the syringe.
4. Inject the saline diluent into the THROMBIN-JMI thrombin vial from the syringe to reconstitute the THROMBIN-JMI thrombin powder.
5. When the THROMBIN-JMI powder is completely dissolved, draw the THROMBIN-JMI thrombin solution into the syringe.
6. Remove the syringe from the transfer device by turning syringe counterclockwise.
7. Affix spray tip by pushing down and turning clockwise until the spray tip locks in place.
8. To spray, depress the syringe plunger in a normal fashion to dispense the THROMBIN-JMI thrombin solution through the tip in a fine spray.
9. Discard unused contents and syringe.

For use of THROMBIN-JMI 5,000 IU Syringe Spray Kit with GEL-FLOW™ NT:

1. Remove the outer lid by pulling up at the indicated edge. The inner tray is sterile and suitable for introduction into any operating field.
2. Remove the cover on the inner tray to expose sterile contents.
3. Using the sterile syringe equipped with a transfer device, draw all of the 5 mL of the saline diluent from the vial into the syringe.
4. Inject the saline diluent into the THROMBIN-JMI thrombin vial from the syringe to reconstitute the THROMBIN-JMI thrombin powder.
5. When the THROMBIN-JMI powder is completely dissolved, draw the THROMBIN-JMI thrombin solution into the syringe.
6. Remove the syringe from the transfer device by turning syringe counterclockwise.
7. DISCARD the SPRAY TIP.
8. Use THROMBIN-JMI thrombin solution syringe according to the directions for use in the GEL-FLOW™ NT package insert.

THROMBIN-JMI EPISTAXIS KIT

Refer to THROMBIN-JMI Epistaxis Kit instructions for accessory assembly and use.

Each epistaxis kit contains one vial of THROMBIN-JMI, one vial of diluent and one nasal drug delivery device.

1. Remove the outer lid by pulling up at the indicated edge. The inner tray is sterile and suitable for introduction into any operating field.
2. Remove the cover on the inner tray to expose sterile contents.
3. Using the sterile syringe equipped with a transfer device, draw the desired amount of saline diluent from the vial into the syringe.
4. Inject the saline diluent into the THROMBIN-JMI thrombin vial from the syringe to reconstitute the THROMBIN-JMI thrombin powder.
5. When the THROMBIN-JMI powder is completely dissolved, draw the THROMBIN-JMI thrombin solution into the syringe.
6. Remove the syringe from the transfer device by turning syringe counterclockwise.
7. Affix the nasal drug delivery device on to the syringe by pushing the device down onto the THROMBIN-JMI thrombin solution filled syringe and turn clockwise until the nasal drug delivery device locks in place.
8. Insert the nasal drug delivery device into the naris and spray the THROMBIN-JMI thrombin solution onto the nasal mucosa through the nasal drug delivery device by depressing the syringe plunger using mild or moderate pressure on the syringe plunger.
9. After administration of THROMBIN-JMI, the device may be removed immediately or briefly held in the nasal passage.
10. Discard the unused contents, nasal drug delivery device, and the syringe.

2.2 Administration

Topical application of THROMBIN-JMI

1. The recipient surface should be sponged (not wiped) free of blood before THROMBIN-JMI is applied.
2. A spray may be used or the surface may be flooded using a sterile syringe and small gauge needle. The most effective hemostasis results occur when the THROMBIN-JMI mixes freely with the blood as soon as it reaches the surface.
3. Sponging of the treated surfaces should be avoided to assure that the clot remains securely in place.

Use in conjunction with Absorbable Gelatin Sponge

Consult the Absorbable Gelatin Sponge, USP labeling for complete information for use prior to utilizing the following thrombin saturated sponge procedure.

1. Prepare THROMBIN-JMI solution to desired strength.
2. Immerse sponge strips of the desired size in THROMBIN-JMI solution. Knead the sponge strips vigorously with moistened, gloved fingers to remove trapped air, thereby facilitating saturation of the sponge.
3. Apply saturated sponge to bleeding area. Hold in place with a pledget of cotton or a small gauze sponge until hemostasis occurs.

Use in conjunction with GEL-FLOW™ NT

THROMBIN-JMI may also be used with GEL-FLOW™ NT according to the directions for use in the GEL-FLOW™ NT package insert.

3 DOSAGE FORMS AND STRENGTHS

THROMBIN-JMI (Thrombin, Topical (Bovine) U.S.P.), Solution for topical use is supplied in the following packages:

Vial: 5,000 IU vial with 5 mL diluent.

Vial: 20,000 IU vial with 20 mL diluent.

THROMBIN-JMI Pump Spray Kit is supplied in the following packages:

Pump Spray Kit: 20,000 IU vial with 20 mL diluent, spray pump and actuator.

THROMBIN-JMI Syringe Spray Kit is supplied in the following packages:

Syringe Spray Kit: 5,000 IU vial with 5 mL diluent, spray tip and syringe.

Syringe Spray Kit: 20,000 IU vial with 20 mL diluent, spray tip and syringe.

THROMBIN-JMI Epistaxis Kit is supplied in the following packages:

5,000 IU vial with 5 mL diluent, nasal drug delivery device and syringe.

THROMBIN-JMI® is supplied in the Gelfoam-JMI™ Kits:

Gelfoam-JMI™ Sponge Kit (Gelfoam® Absorbable Gelatin Sponge, USP and Thrombin, Topical (Bovine) U.S.P., THROMBIN-JMI®, 5,000 IU vial with 5 mL diluent).
Gelfoam-JMI™ Powder Kit (Gelfoam® Absorbable Gelatin Powder and Thrombin, Topical (Bovine) U.S.P., THROMBIN-JMI®, 5,000 IU with 5 mL diluent).

THROMBIN-JMI® 5,000 IU Syringe Spray Kit is supplied in the GEL- FLOW™ Kit:

GEL-FLOW™ Kit (GEL-FLOW™ NT Absorbable Gelatin Powder and Thrombin, Topical (Bovine) U.S.P., THROMBIN-JMI®, 5,000 IU Syringe Spray Kit).

4 CONTRAINDICATIONS

- Do not inject directly into the circulatory system. Because of its action in the clotting mechanism, THROMBIN-JMI can cause extensive intravascular clotting or death.
- Do not re-expose patients to THROMBIN-JMI if there are known or suspected antibodies to bovine thrombin and/or factor V.
- Do not administer to patients with a history of hypersensitivity to THROMBIN-JMI, its components and/or to material of bovine origin.
- Do not use for treatment of severe or brisk arterial bleeding.

5 WARNINGS AND PRECAUTIONS

5.1 Hypersensitivity Reactions

- Allergic reactions, including anaphylactic/anaphylactoid reactions, have been reported following administration of THROMBIN-JMI.
- Institute intensive supportive measures and treat individual symptoms. Secure the airway and establish adequate respiratory exchange.

5.2 Thrombosis

THROMBIN-JMI causes thrombosis if it enters the circulatory system due to its action in the clotting system.

Apply topically. DO NOT INJECT.

5.3 Immunogenicity

Inhibitory antibodies may develop in patients and interfere with hemostasis. Do not re-expose patients to THROMBIN-JMI if there are known or suspected antibodies to bovine thrombin and/or factor V, due to the potential for these antibodies to interfere with hemostasis. Monitor patients for abnormal coagulation laboratory values, bleeding, or thrombosis.

Bleeding

Bleeding may result from the development of antibodies against factor V. These antibodies may cross-react with human factor V and lead to human factor V deficiency.

Thrombosis

Thrombosis may result from the development of antibodies against bovine thrombin.

6 ADVERSE REACTIONS

The most common adverse reactions (incidence greater than or equal to 2%) following administration of THROMBIN-JMI were: hypersensitivity, bleeding, anemia, post-operative wound infection, thromboembolic events, hypotension, pyrexia, tachycardia and thrombocytopenia.

6.1 Clinical Trials Experience

Because clinical trials are conducted under widely varying conditions, adverse reaction rates observed in the clinical trials of a drug cannot be directly compared to rates in the clinical trials of another drug and may not reflect the rates observed in practice.

The safety assessment of THROMBIN-JMI is based primarily on the review of post marketing publications summarizing four (4) randomized controlled clinical trials in which THROMBIN-JMI was used as a comparator^2–5, and one (1) observational study^6 [see Clinical Studies (14)].

Study 1

In a randomized, double-blinded, controlled trial that compared recombinant human thrombin to THROMBIN-JMI, 206 patients received THROMBIN-JMI and 205 patients received recombinant human thrombin as adjuncts to hemostasis in liver resection, spine, peripheral arterial bypass, and dialysis access surgeries.^2 Four hundred one (401) patients completed the trial. The reported adverse reactions in both treatment groups were: cardiac events (18%), hypersensitivity (17%), other infections (15%), bleeding (11%), postoperative wound infection (10%), and thromboembolic events (5%). Among 200 patients who were evaluated for the presence of antibodies to THROMBIN-JMI, 10 patients (5%) were positive at baseline and 43 (21.5%) after treatment. The seroconversion rate in THROMBIN-JMI group was 18.4%.

Study 2

In a multicenter, prospective, randomized, double-blinded, controlled trial that compared plasma-derived human thrombin to THROMBIN-JMI, 152 patients received THROMBIN-JMI and 153 patients received human thrombin applied topically to the target bleeding site with a gelatin sponge.^3 Serious adverse reactions (pyrexia and post-procedural hematoma) were reported in two patients receiving THROMBIN-JMI. In this study, 16 out of 126 (12.7%) patients who received THROMBIN-JMI demonstrated seroconversion for at least one of the four antibodies assayed. The four separate ELISA assays used to detect development of antibodies and the corresponding antibody development rates included: 1) Anti-bovine thrombin 10/126 (7.94%), 2) Anti-bovine factor V/Va 12/126 (9.52%), 3) Anti-human thrombin 3/126 (2.38%) and 4) Anti-human factor V/Va 0/126 (0%).

Study 3

The effect of repeat exposure was evaluated in a multi-center, prospective, randomized, double-blinded, controlled trial on 72 patients with diabetic foot ulcers, using a gel prepared with THROMBIN-JMI and autologous platelet rich plasma that was applied weekly for 12 weeks.^4 Forty (40) patients were treated with the gel at fourteen (14) sites. Safety parameters were evaluated during the 12 weeks of treatment and the three-month follow-up period. No serious adverse reactions related to the gel treatment were reported.

Study 4

In a prospective, randomized, phase 2, non-inferiority study, topical human thrombin was compared with THROMBIN-JMI during vascular, hepatic, soft tissue, and spinal open surgery procedures.^5 A total of 205 patients were randomized in a 2:1 ratio to receive human thrombin (n=137) or THROMBIN-JMI (n=68). The most common treatment-emergent adverse reactions (experienced by >5% patients within a treatment group) were procedural pain, nausea, constipation, pruritus, muscle spasms, insomnia, pyrexia, and vomiting. Two patients in the THROMBIN-JMI group (3.2% of treated patients) showed low-level titers of antibodies to bovine factor V.

6.2 Postmarketing Experience

The following serious adverse reactions have been identified during post approval use of THROMBIN-JMI: anaphylactic reactions, prolonged prothrombin time, prolonged activated partial thromboplastin time, disseminated intravascular coagulation, factor V deficiency, post-procedural hematoma, swelling and Staphylococcal wound infection. Because these reactions are reported voluntarily from a population of uncertain size, it is not always possible to reliably estimate their frequency or establish a causal relationship to drug exposure.

8 USE IN SPECIFIC POPULATIONS

8.1 Pregnancy

Risk Summary

Animal reproduction studies have not been conducted with THROMBIN-JMI. It is also not known whether THROMBIN-JMI can cause fetal harm when administered to a pregnant woman. THROMBIN-JMI should be given to a pregnant woman only if clearly needed.

The estimated background risk of major birth defects and miscarriage for the indicated population is unknown. All pregnancies have a risk of birth defect, loss, or other adverse outcomes. In the U.S. general population, the estimated background risk of major birth defects and miscarriage in clinically recognized pregnancies is 2% to 4% and 15% to 20%, respectively.

8.2 Lactation

It is not known whether this drug is excreted in human milk. The developmental and health benefits of breastfeeding should be considered along with the mother's clinical need for THROMBIN-JMI and any potential adverse effects on the breastfed infant from THROMBIN-JMI or from the underlying maternal condition.

8.4 Pediatric Use

Safety and effectiveness in children have not been established.

8.5 Geriatric Use

Clinical studies of THROMBIN-JMI did not include sufficient numbers of subjects aged 65 and over to determine whether they respond differently from younger subjects. Other reported clinical experience has not identified differences in responses between the elderly and younger patients. In general, dose selection for an elderly patient should be cautious, usually starting at the low end of the dosing range, reflecting the greater frequency of decreased hepatic, renal, or cardiac function, and of concomitant disease or other drug therapy.

11 DESCRIPTION

THROMBIN-JMI, Thrombin, Topical (Bovine), is a protein substance produced through a conversion reaction in which prothrombin of bovine origin is activated by tissue thromboplastin of bovine origin in the presence of calcium chloride. It is supplied as a sterile powder that has been freeze-dried in the final container. Also contained in the preparation are mannitol and sodium chloride. Mannitol is included to make the dried product friable and more readily soluble. The product contains no preservative.

THROMBIN-JMI undergoes multistep chromatographic purification and ultrafiltration. The manufacturing process for THROMBIN-JMI has been further improved by the addition of viral filtration and impurity reduction processes. Analytical studies demonstrate the capability of the current manufacturing process to remove significant amounts of extraneous proteins, and result in a reduction of factor Va light chain content to levels below the limit of detection of semi-quantitative Western Blot assay (<92 ng/mL, when reconstituted as directed). The clinical relevance of these findings is unknown.

12 CLINICAL PHARMACOLOGY

12.1 Mechanism of Action

THROMBIN-JMI requires no intermediate physiological agent for its action. It activates platelets and catalyzes the conversion of fibrinogen to fibrin, which are essential steps for clot formation. Failure to clot blood occurs in the case where the primary clotting defect is the absence of fibrinogen itself. The speed with which thrombin clots blood is dependent upon the concentration of both thrombin and fibrinogen.

13 NONCLINICAL TOXICOLOGY

13.1 Carcinogenesis, Mutagenesis, Impairment of Fertility

No studies have been undertaken examining carcinogenicity, genetic toxicity or fertility.

13.2 Animal Toxicology and/or Pharmacology

Thrombin Concentration Study

In a blinded pre-clinical study conducted on a liver lesion model in swine, an inverse dose related response was observed between the visual bleeding scores and the thrombin [THROMBIN-JMI (Thrombin, Topical (Bovine) U.S.P.) was used for all thrombin concentrations tested in this study.] concentration within the absorbable gelatin powder delivery system (GEL-FLOW™ NT) syringe, a device containing 550 mg of absorbable gelatin powder (GELFOAM® Powder).^1 Bleeding was assigned scores according to a visual scale, with scores of 0 (no bleeding), 0.5 (ooze), 1 (very slight), 2 (slight), 3 (moderate), and 4 (severe). Scores of 1 and less were considered clinically acceptable. The 770 IU/mL thrombin concentration provided statistically significant lower bleeding scores than either 375 IU/mL or 250 IU/mL thrombin concentrations [Per the THROMBIN-JMI prescribing information, for routine use THROMBIN-JMI is reconstituted with sterile isotonic saline at a recommended concentration of 1,000 to 2,000 IU per mL.] (Table 1). The results of this study showed that higher concentrations of thrombin within the GEL-FLOW™ NT syringe resulted in improved hemostasis as measured by lower bleeding scores.

Table 1: Comparison of Effect on Hemostasis of Varying Thrombin Concentrations in GEL-FLOW™ NT as Measured by Bleeding Scores in Swine Liver Lesion Model using Repeated Measures Logistic Regression
Parameter | 250 IU/mL Mean (Standard Error) | 375 IU/mL Mean (Standard Error) | 770 IU/mL Mean (Standard Error)
3 Minute Bleeding Score | 1.8 (0.2) | 1.6 (0.2) | 0.7 (0.2) [Significantly different from both 250 and 375 IU/mL at <0.001 significance level. Tukey adjusted p-values for multiple comparisons.]
6 Minute Bleeding Score | 1.7 (0.2) | 1.5 (0.2) | 0.6 (0.2)
9 Minute Bleeding Score | 1.5 (0.2) | 1.2 (0.2) | 0.5 (0.2)
12 Minute Bleeding Score | 1.4 (0.2) | 1.0 (0.2) [Significantly different from 250 IU/mL at the 0.05 significance level. Tukey adjusted p-value for multiple comparisons.] | 0.4 (0.2)

14 CLINICAL STUDIES

Observational Study

A total of 554 subjects were enrolled, in a multicenter, open-label, observational study (MOSAIC) conducted to assess the effect of possible exposure to THROMBIN-JMI on activated partial thromboplastin time (aPTT) at 48 hours post-surgery in subjects with likelihood of prior exposure to THROMBIN-JMI within the past 4 years.^6 Of the 554 subjects, 550 had undergone surgery and completed the study. A total of 384 subjects undergoing vascular surgeries, neurosurgeries and orthopedic surgeries were exposed to THROMBIN-JMI (5,000 to 20,000 IU).

In this study, the impact of exposure to THROMBIN-JMI in 78 subjects who were positive for anti-bovine thrombin (aBT) antibodies prior to surgery was compared with 140 subjects who did not have any aBT antibodies and were not exposed to THROMBIN-JMI. The study did not meet the pre-specified primary endpoint, a mean change from baseline in aPTT at 48 hours post-surgery. The study was not powered to detect coagulopathy related to an immune response after bovine thrombin use.

A post hoc analysis was performed in which subjects who underwent surgery were re-assigned to one of four exploratory cohorts based on the presence or absence of pre-surgery anti-bovine factor V/anti-bovine factor V active (aBV/Va) antibodies and whether or not they were administered THROMBIN-JMI during the study surgery. Non-inferiority (based on aPTT) was observed in these exploratory cohorts at all-time points of 48 hours, 4 weeks, and 8 weeks post-surgery.

For the primary study cohort (THROMBIN-JMI use in subjects with baseline positive aBT or positive aBV/Va), there was a higher incidence of seroconversion from anti human thrombin (aHT) negative at baseline to post-surgery positive compared to the primary reference cohort (no THROMBIN-JMI use in subjects with baseline negative aBT or negative aBV/Va). This difference was not present at 48 hours after surgery but was evident at 4 weeks and 8 weeks post-surgery. A similar immunological response with aBT and aBV/Va antibodies was observed following THROMBIN-JMI administration.

Secondary immune responses in patients treated with THROMBIN-JMI were evidenced by the generation of anti-bovine and anti-human thrombin and factor V/Va antibodies, consistent with known immunogenicity of topical bovine thrombin.

15 REFERENCES

1. Morse DC, Silva E, Bartrom J, et al: Improved bleeding scores using Gelfoam Powder with incremental concentrations of bovine thrombin in a swine liver lesion model. J Throm Thrombolysis. 2016;42(3):352–359.
2. Chapman WC, Singla N, Genyk Y, et al: A Phase 3, Randomized, Double-Blind Comparative Study of the Efficacy and Safety of Topical Recombinant Human Thrombin and Bovine Thrombin in Surgical Hemostasis. J Am Coll Surg. 2007;205:256–265.
3. Doria C, Fischer CP, Wood CG, et al: Phase 3, randomized, double-blind study of plasma-derived human thrombin versus bovine thrombin in achieving hemostasis in patients undergoing surgery. Curr Med Res Opin. 2008;24(3):785–794.
4. Driver VR, Hanft J, Fylling CP, et al: A Prospective, Randomized, Controlled Trial of Autologous Platelet-Rich Plasma Gel for the Treatment of Diabetic Foot Ulcers. Ostomy/Wound Management. 2006;52(6):68–87.
5. Minkowitz H, Navarro-Puerto J, Lakshman S, et al: Prospective, Randomized, Phase II, Non-Inferiority Study to Evaluate the Safety and Efficacy of Topical Thrombin (Human) Grifols as Adjunct to Hemostasis During Vascular, Hepatic, Soft Tissue, and Spinal Open Surgery. J Am Coll Surg. 2019;229(5):497–507.
6. Paterson CA, Pixton GC, Proskin HM, et al: Immune responses associated with perioperative exposure and reexposure to topical bovine thrombin do not impair hemostasis. Clin Appl Thromb Hemost. 2011;17(6):620–632.

16 HOW SUPPLIED/STORAGE AND HANDLING

Not made with natural rubber latex.

THROMBIN-JMI® is supplied in the following packages:

NDC 60793-215-05

Vial: 5,000 IU vial with 5 mL diluent.
NDC 60793-217-20
Vial: 20,000 IU vial with 20 mL diluent.

THROMBIN-JMI® Pump Spray Kit is supplied in the following package:

NDC 60793-217-21

Pump Spray Kit: 20,000 IU vial with 20 mL diluent, spray pump and actuator.

THROMBIN-JMI® Syringe Spray Kit is supplied in the following packages:

NDC 60793-705-05

Syringe Spray Kit: 5,000 IU vial with 5 mL diluent, spray tip and syringe.
  NDC 60793-217-22
Syringe Spray Kit: 20,000 IU vial with 20 mL diluent, spray tip and syringe.

THROMBIN-JMI® Epistaxis Kit is supplied in the following package:

NDC 60793-205-05

Epistaxis Kit: 5,000 IU vial with 5 mL diluent, nasal drug delivery device and syringe.

THROMBIN-JMI® is supplied in the Gelfoam-JMI™ Kits:

GTIN 00360793310107 (60793-310-10)
Gelfoam-JMI™ Sponge Kit (Gelfoam® Absorbable Gelatin Sponge, USP and Thrombin, Topical (Bovine) U.S.P., THROMBIN-JMI®, 5,000 IU vial with 5 mL diluent).
GTIN 00360793410104 (60793-410-10)
Gelfoam-JMI™ Powder Kit (Gelfoam® Absorbable Gelatin Powder and Thrombin, Topical (Bovine) U.S.P., THROMBIN-JMI®, 5,000 IU with 5 mL diluent).

THROMBIN-JMI® 5,000 IU Syringe Spray Kit is supplied in the GEL- FLOW™ Kit:

GTIN 00300092250018
GEL-FLOW™ Kit (GEL-FLOW™ NT Absorbable Gelatin Powder and Thrombin, Topical (Bovine) U.S.P., THROMBIN-JMI®, 5,000 IU Syringe Spray Kit).

STORAGE AND HANDLING

Store THROMBIN-JMI at 2°C – 25°C (36°F – 77°F).

17 PATIENT COUNSELING INFORMATION

Because THROMBIN-JMI may cause the formation of clots in blood vessels if it enters the bloodstream, advise patients to consult their physician if they experience leg tenderness or swelling, chest pain, shortness of breath, or difficulty speaking or swallowing.

Manufactured by: GenTrac, Incorporated, Middleton, Wisconsin 53562

Distributed by Pfizer Inc, New York, New York 10001

US License No. 977

LAB-0604-14.0

PRINCIPAL DISPLAY PANEL - 5,000 IU Vial Label

NDC 60793-315-01

THROMBIN,
TOPICAL
(BOVINE), U.S.P.
THROMBIN-JMI®

5,000 International Units

Pfizer

Rx Only

PRINCIPAL DISPLAY PANEL - 5 mL Vial Label

NDC 60793-218-09

SODIUM
CHLORIDE

U.S.P. 0.9% for
THROMBIN, TOPICAL
(BOVINE), U.S.P.
THROMBIN-JMI®

5 mL

Pfizer

Rx Only

PRINCIPAL DISPLAY PANEL - 5000 IU Vial Kit Carton

FOR TOPICAL USE ONLY – DO NOT INJECT

THROMBIN, TOPICAL (BOVINE), U.S.P.
THROMBIN-JMI®

5,000 International Units

CONTAINS NO PRESERVATIVE
STORE AT 2-25°C (36-77°F)
SEE PACKAGE INSERT FOR COMPLETE DIRECTIONS

CONTENTS:

ONE VIAL 5,000
UNITS THROMBIN

ONE VIAL 5 mL
DILUENT

ONE TRANSFER
DEVICE

Pfizer

PRINCIPAL DISPLAY PANEL - 20,000 IU Vial Label

NDC 60793-317-01

THROMBIN,
TOPICAL
(BOVINE), U.S.P.
THROMBIN-JMI®

20,000
International Units

Pfizer

Rx Only

PRINCIPAL DISPLAY PANEL - 20 mL Vial Label

NDC 60793-221-09

SODIUM
CHLORIDE

U.S.P. 0.9% for
THROMBIN, TOPICAL (BOVINE), U.S.P.
THROMBIN-JMI®

20 mL

Pfizer

Rx Only

PRINCIPAL DISPLAY PANEL- 20,000 IU Vial Kit Carton

FOR TOPICAL USE ONLY – DO NOT INJECT

THROMBIN, TOPICAL (BOVINE), U.S.P.
THROMBIN-JMI®

20,000 International Units

CONTAINS NO PRESERVATIVE
STORE AT 2-25°C (36-77°F)
SEE PACKAGE INSERT FOR COMPLETE DIRECTIONS

CONTENTS:

ONE VIAL 20,000
UNITS THROMBIN

ONE VIAL 20 mL
DILUENT

ONE TRANSFER
DEVICE

Pfizer

PRINCIPAL DISPLAY PANEL - 20,000 IU Pump Spray Kit Tray

FOR TOPICAL USE ONLY – DO NOT INJECT

NDC 60793-217-21

THROMBIN, TOPICAL (BOVINE), U.S.P.
THROMBIN-JMI®

20,000 International Units

CONTAINS NO PRESERVATIVE
STORE AT 2-25°C (36-77°F)
SEE PACKAGE INSERT FOR COMPLETE DIRECTIONS
NOT MADE WITH NATURAL RUBBER LATEX.

Rx Only

PUMP SPRAY KIT
CONTENTS – STERILE UNLESS TRAY IS OPENED OR DAMAGED:

ONE VIAL 20,000
UNITS THROMBIN

ONE VIAL
20 mL DILUENT

ONE TRANSFER
DEVICE

ONE SPRAY PUMP
AND ACTUATOR

Pfizer

PAA108460

Manufactured by: GenTrac, Incorporated,
Middleton, Wisconsin 53562
Distributed by Pfizer Inc,
New York, NY 10017
US License No. 977

PRINCIPAL DISPLAY PANEL - 20,000 IU Pump Spray Kit Carton

FOR TOPICAL USE ONLY – DO NOT INJECT

THROMBIN, TOPICAL (BOVINE), U.S.P.
THROMBIN-JMI®

NDC 60793-217-21

20,000 International Units

CONTAINS NO PRESERVATIVE
STORE AT 2-25°C (36-77°F)
SEE PACKAGE INSERT FOR COMPLETE DIRECTIONS
NOT MADE WITH NATURAL RUBBER LATEX.

Rx Only

PUMP SPRAY KIT
CONTENTS – STERILE UNLESS TRAY IS OPENED OR DAMAGED:

ONE VIAL 20,000
UNITS THROMBIN

ONE VIAL
20 mL DILUENT

ONE TRANSFER
DEVICE

ONE SPRAY PUMP
AND ACTUATOR

Pfizer

PRINCIPAL DISPLAY PANEL - 20,000 IU Syringe Spray Kit Tray

FOR TOPICAL USE ONLY – DO NOT INJECT

NDC 60793-217-22

THROMBIN, TOPICAL (BOVINE), U.S.P.
THROMBIN-JMI®

20,000 International Units

CONTAINS NO PRESERVATIVE
STORE AT 2-25°C (36-77°F)
SEE PACKAGE INSERT FOR COMPLETE DIRECTIONS
NOT MADE WITH NATURAL RUBBER LATEX.

Rx Only

SYRINGE SPRAY KIT
CONTENTS – STERILE UNLESS TRAY IS OPENED OR DAMAGED:

ONE VIAL 20,000
UNITS THROMBIN

ONE VIAL
20 mL DILUENT

ONE TRANSFER
DEVICE

ONE STERILE DISPOSABLE SYRINGE
WITH SPRAY TIP

Pfizer

PAA108466

Manufactured by: GenTrac, Incorporated,
Middleton, Wisconsin 53562
Distributed by Pfizer Inc,
New York, NY 10017
US License No. 977

PRINCIPAL DISPLAY PANEL - 20,000 IU Syringe Spray Kit Carton

FOR TOPICAL USE ONLY – DO NOT INJECT

THROMBIN, TOPICAL (BOVINE), U.S.P.
THROMBIN-JMI®

NDC 60793-217-22

20,000 International Units

CONTAINS NO PRESERVATIVE
STORE AT 2-25°C (36-77°F)
SEE PACKAGE INSERT FOR COMPLETE DIRECTIONS
NOT MADE WITH NATURAL RUBBER LATEX.

Rx Only

SYRINGE SPRAY KIT
CONTENTS – STERILE UNLESS TRAY IS OPENED OR DAMAGED:

ONE VIAL 20,000
UNITS THROMBIN

ONE VIAL
20 mL DILUENT

ONE TRANSFER
DEVICE

ONE STERILE DISPOSABLE SYRINGE
WITH SPRAY TIP

Pfizer

PRINCIPAL DISPLAY PANEL - 5,000 IU Syringe Spray Kit Tray

FOR TOPICAL USE ONLY – DO NOT INJECT

NDC 60793-705-05

THROMBIN, TOPICAL (BOVINE), U.S.P.
THROMBIN-JMI®

5,000 International Units

CONTAINS NO PRESERVATIVE
STORE AT 2-25°C (36-77°F)
SEE PACKAGE INSERT FOR COMPLETE DIRECTIONS
NOT MADE WITH NATURAL RUBBER LATEX.

Rx Only

SYRINGE SPRAY KIT
CONTENTS – STERILE UNLESS TRAY IS OPENED OR DAMAGED:

ONE VIAL 5,000
UNITS THROMBIN

ONE VIAL
5 mL DILUENT

ONE TRANSFER
DEVICE

ONE STERILE DISPOSABLE SYRINGE
WITH SPRAY TIP

Pfizer

PAA108453

Manufactured by: GenTrac, Incorporated,
Middleton, Wisconsin 53562
Distributed by Pfizer Inc,
New York, NY 10017
US License No. 977

PRINCIPAL DISPLAY PANEL - 5,000 IU Syringe Spray Kit Carton

FOR TOPICAL USE ONLY – DO NOT INJECT

THROMBIN, TOPICAL (BOVINE), U.S.P.
THROMBIN-JMI®

NDC 60793-705-05

5,000 International Units

CONTAINS NO PRESERVATIVE
STORE AT 2-25°C (36-77°F)
SEE PACKAGE INSERT FOR COMPLETE DIRECTIONS
NOT MADE WITH NATURAL RUBBER LATEX.

Rx Only

SYRINGE SPRAY KIT
CONTENTS – STERILE UNLESS TRAY IS OPENED OR DAMAGED:

ONE VIAL 5,000
UNITS THROMBIN

ONE VIAL
5 mL DILUENT

ONE TRANSFER
DEVICE

ONE STERILE DISPOSABLE SYRINGE
WITH SPRAY TIP*

* For use of Thrombin-JMI Thrombin solution with GEL-FLOW™ NT, discard spray tip and use Thrombin-JMI Thrombin solution syringe according to the directions for use in
the GEL-FLOW™ NT package insert.

Pfizer

PRINCIPAL DISPLAY PANEL - 5,000 IU Epistaxis Kit Tray

FOR TOPICAL USE ONLY – DO NOT INJECT

NDC 60793-205-05

THROMBIN, TOPICAL (BOVINE), U.S.P.
THROMBIN-JMI®

5,000 International Units

CONTAINS NO PRESERVATIVE
STORE AT 2-25°C (36-77°F)
SEE PACKAGE INSERT FOR COMPLETE DIRECTIONS
NOT MADE WITH NATURAL RUBBER LATEX.

Rx Only

EPISTAXIS KIT
CONTENTS – STERILE UNLESS TRAY IS OPENED OR DAMAGED:

ONE VIAL 5,000
UNITS THROMBIN

ONE VIAL
5 mL DILUENT

ONE TRANSFER
DEVICE

ONE STERILE DISPOSABLE SYRINGE
WITH NASAL DRUG DELIVERY DEVICE

Pfizer

PAA108463

Manufactured by: GenTrac, Incorporated,
Middleton, Wisconsin 53562
Distributed by Pfizer Inc,
New York, NY 10017
US License No. 977

PRINCIPAL DISPLAY PANEL - 5,000 IU Epistaxis Kit Carton

FOR TOPICAL USE ONLY – DO NOT INJECT

THROMBIN, TOPICAL (BOVINE), U.S.P.
THROMBIN-JMI®

NDC 60793-205-05

5,000 International Units

CONTAINS NO PRESERVATIVE
STORE AT 2-25°C (36-77°F)
SEE PACKAGE INSERT FOR COMPLETE DIRECTIONS
NOT MADE WITH NATURAL RUBBER LATEX.

Rx Only

EPISTAXIS KIT
CONTENTS – STERILE UNLESS TRAY IS OPENED OR DAMAGED:

ONE VIAL 5,000
UNITS THROMBIN

ONE VIAL
5 mL DILUENT

ONE TRANSFER
DEVICE

ONE STERILE DISPOSABLE SYRINGE
WITH NASAL DRUG DELIVERY DEVICE

Pfizer